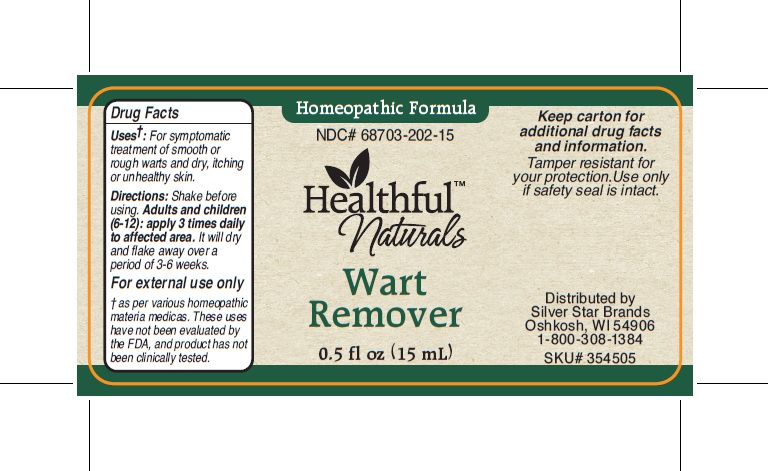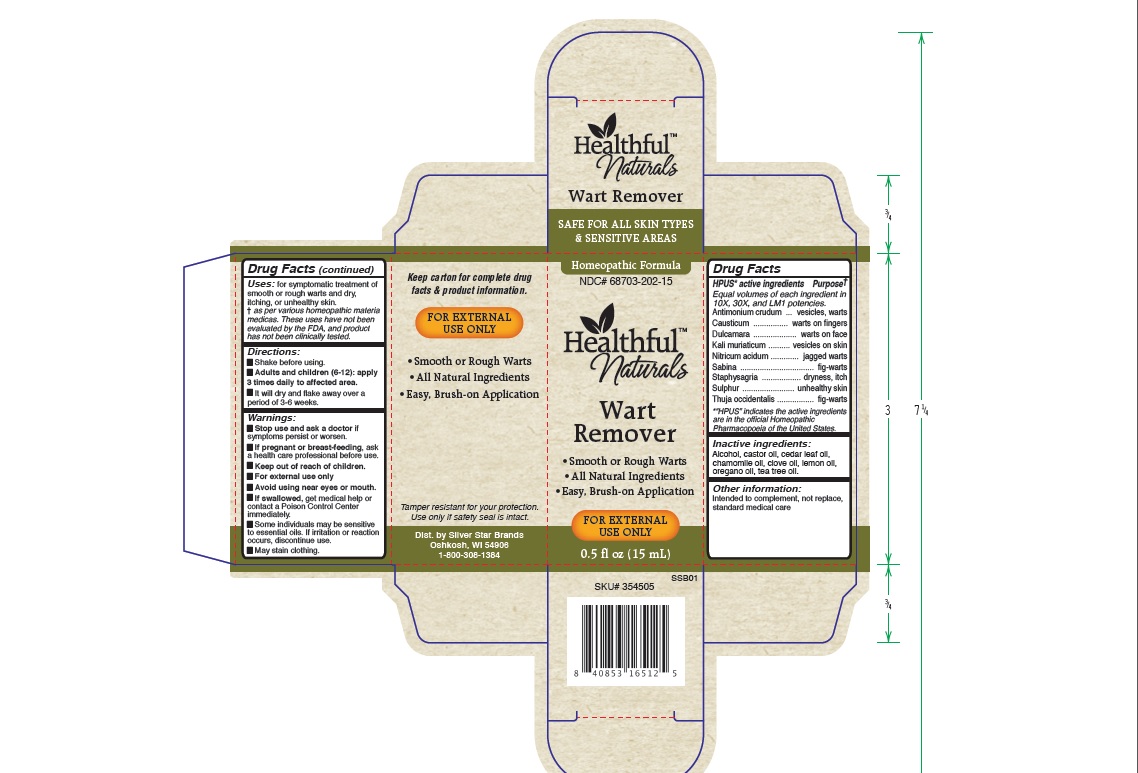 DRUG LABEL: Healthful Naturals Wart Remover
NDC: 68703-202 | Form: LIQUID
Manufacturer: Silver Star Brands
Category: homeopathic | Type: HUMAN OTC DRUG LABEL
Date: 20240114

ACTIVE INGREDIENTS: ANTIMONY TRISULFIDE 10 [hp_X]/15 mL; CAUSTICUM 10 [hp_X]/15 mL; SOLANUM DULCAMARA TOP 10 [hp_X]/15 mL; NITRIC ACID 10 [hp_X]/15 mL; JUNIPERUS SABINA LEAFY TWIG 10 [hp_X]/15 mL; DELPHINIUM STAPHISAGRIA SEED 10 [hp_X]/15 mL; SULFUR 10 [hp_X]/15 mL; THUJA OCCIDENTALIS LEAFY TWIG 10 [hp_X]/15 mL
INACTIVE INGREDIENTS: MATRICARIA CHAMOMILLA FLOWERING TOP OIL; TEA TREE OIL; CEDAR LEAF OIL; CLOVE OIL; LEMON OIL; OREGANO LEAF OIL; .ALPHA.-ISOBUTYLPHENETHYL ALCOHOL; CASTOR OIL

Healthful Naturals Wart Remover

HPUS active ingredients:

Antimonium crudum, Causticum, Dulcamara, Kali muriaticum, Nitricum acidum, Sabina, Staphysagria, Sulphur, Thuja occidentalis. Equal volumes of each ingredient in 10X, 30X, and LM1 potencies. “HPUS”indicates the active ingredients are in the official Homeopathic Pharmacopeia of the United States.

USES

for symptomatic treatment of smooth or rough warts and dry, itching or unhealthy skin.

†as per various homeopathic materia medicas. These uses have not been evaluated by the FDA, and product has not been clinically tested.

Warnings

Stop use and ask your doctor if symptoms persist or worsen.

If pregnant or breast-feeding, ask a healthcare professional before use.

Keep out of reach of children.

For external use only.

Avoid using near eyes or mouth.

If swallowed, get medical help or contact a Poison Control Center immediately.

Some individuals may be sensitive to essential oils. If irritation or reaction occurs, discontinue use.

May stain clothing.

Directions

Shake before using. • Adults and children (6-12): apply 3 times daily to affected area. • It will dry and flake away over a period of 3-6 weeks.

For external use only

Other information:

Intended to complement, not replace, standard medical care. Tamper resistant for your protection. Use only if safety seal is intact.

INACTIVE INGREDIENT

Alcohol, castor oil, cedar leaf oil, chamomile oil, clove oil, lemon oil, oregano oil, tea tree oil.

HPUS* active ingredients Purpose†

Equal volumes of each ingredient in 10X, 30X, and LM1 potencies.

Antimonium crudum............................................vesicles, warts

Causticum........................................................warts on fingers

Dulcamara...........................................................warts on face

Kali muriaticum..................................................vesicles on skin

Nitricum acidum.....................................................jagged warts

Sabina........................................................................fig-warts

Staphysagria..........................................................dryness, itch

Sulphur...............................................................unhealthy skin

Thuja occidentalis.........................................................fig-warts

“HPUS”indicates the active ingredients are in the official Homeopathic Pharmacopeia of the United States.

Keep out of reach of children